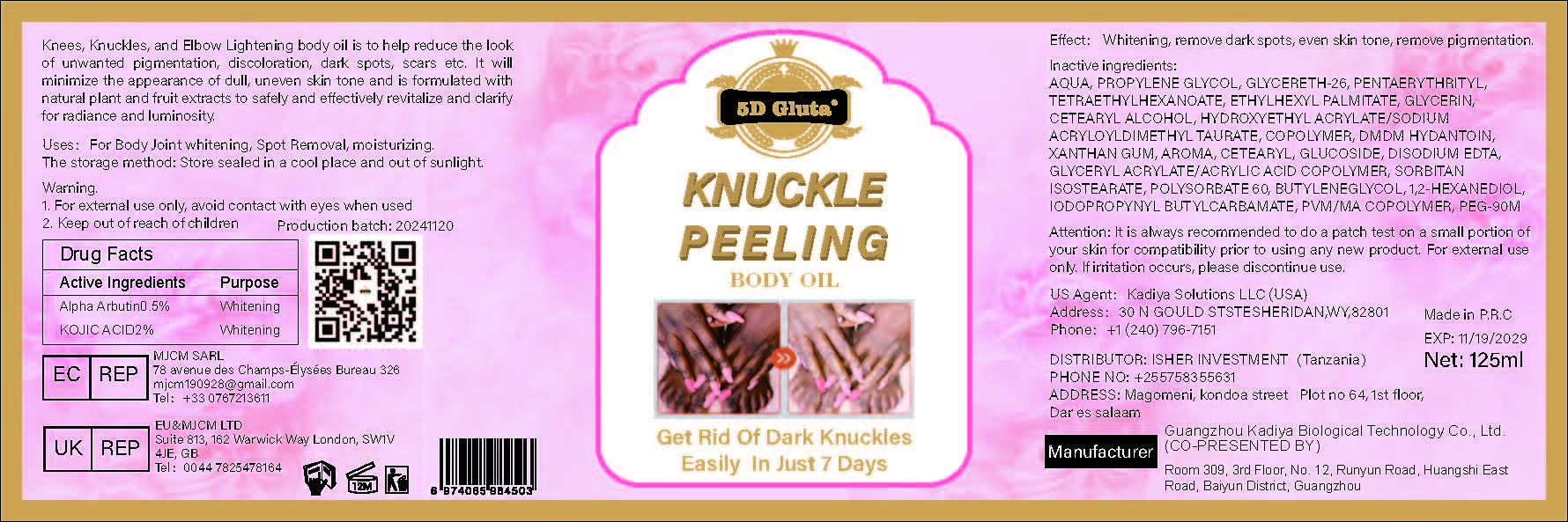 DRUG LABEL: KNUCKLEPEELINGBODYOIL
NDC: 84423-065 | Form: CREAM, AUGMENTED
Manufacturer: Guangzhou Kadiya Biotechnology Co., Ltd.
Category: otc | Type: HUMAN OTC DRUG LABEL
Date: 20250217

ACTIVE INGREDIENTS: KOJIC ACID 2.5 g/125 mL; ALPHA-ARBUTIN 0.625 g/125 mL
INACTIVE INGREDIENTS: PENTAERYTHRITYL TETRAETHYLHEXANOATE; AQUA; PROPYLENE GLYCOL; 1,3-BUTYLENEGLYCOL DIMETHACRYLATE; IODOPROPYNYL BUTYLCARBAMATE; CETEARYL GLUCOSIDE; ETHYLHEXYL PALMITATE; DMDM HYDANTOIN; SORBITAN ISOSTEARATE; GLYCERETH-26; PEG-90M; GLYCERIN; XANTHAN GUM; POLYSORBATE 60; GLYCERYL ACRYLATE/ACRYLIC ACID COPOLYMER (300000 CP AT 2%); KOJIC DIPALMITATE; EDETATE DISODIUM; 1,2-HEXANEDIOL; CETEARYL ALCOHOL; METHYL VINYL ETHER AND MALEIC ANHYDRIDE COPOLYMER (1100000 WAMW); HYDROXYETHYL ACRYLATE/SODIUM ACRYLOYLDIMETHYL TAURATE COPOLYMER (45000 MPA.S AT 1%)

PURPOSE

For Body Joint whitening, Spot Removal, moisturizing

INACTIVE INGREDIENT

AQUA，PROPYLENE GLYCOL，GLYCERETH-26，PENTAERYTHRITYL，TETRAETHYLHEXANOATE，ETHYLHEXYL PALMITATE，GLYCERIN，CETEARYL ALCOHOL，HYDROXYETHYL ACRYLATE/SODIUM ACRYLOYLDIMETHYL TAURATE，COPOLYMER，DMDM HYDANTOIN，XANTHAN GUM，AROMA，CETEARYL，GLUCOSIDE，DISODIUM EDTA，GLYCERYL ACRYLATE/ACRYLIC ACID COPOLYMER，SORBITAN ISOSTEARATE，POLYSORBATE 60，BUTYLENEGLYCOL，1,2-HEXANEDIOL，IODOPROPYNYL BUTYLCARBAMATE，PVM/MA COPOLYMER，PEG-90M

Warning.
1、For external use only, avoid contact with eyes when used
2、Keep out of reach of children

INDICATIONS AND USAGE

Whitening, remove dark spots, even skin tone, remove pigmentation.

DOSAGE AND ADMINISTRATION

Knees, Knuckles, and Elbow Lightening body oil is to help reduce the look of unwanted pigmentation, discoloration, dark spots, scars etc. It will minimize the appearance of dull, uneven skin tone and is formulated with natural plant and fruit extracts to safely and effectively revitalize and clarify for radiance and luminosity.

KEEP OUT OF REACH OF CHILDREN SECTION

Active Ingredients
Alpha Arbutin0.5%
KOJIC ACID2%

PACKAGE LABEL

Active Ingredients
Alpha Arbutin0.5%
KOJIC ACID2%

Uses：
For Body Joint whitening, Spot Removal, moisturizing
The storage method：
Store sealed in a cool place and out of sunlight

Warning.
1、For external use only, avoid contact with eyes when used
2、Keep out of reach of children

Inactive ingredients：
AQUA，PROPYLENE GLYCOL，GLYCERETH-26，PENTAERYTHRITYL，TETRAETHYLHEXANOATE，ETHYLHEXYL PALMITATE，GLYCERIN，CETEARYL ALCOHOL，HYDROXYETHYL ACRYLATE/SODIUM ACRYLOYLDIMETHYL TAURATE，COPOLYMER，DMDM HYDANTOIN，XANTHAN GUM，AROMA，CETEARYL，GLUCOSIDE，DISODIUM EDTA，GLYCERYL ACRYLATE/ACRYLIC ACID COPOLYMER，SORBITAN ISOSTEARATE，POLYSORBATE 60，BUTYLENEGLYCOL，1,2-HEXANEDIOL，IODOPROPYNYL BUTYLCARBAMATE，PVM/MA COPOLYMER，PEG-90M